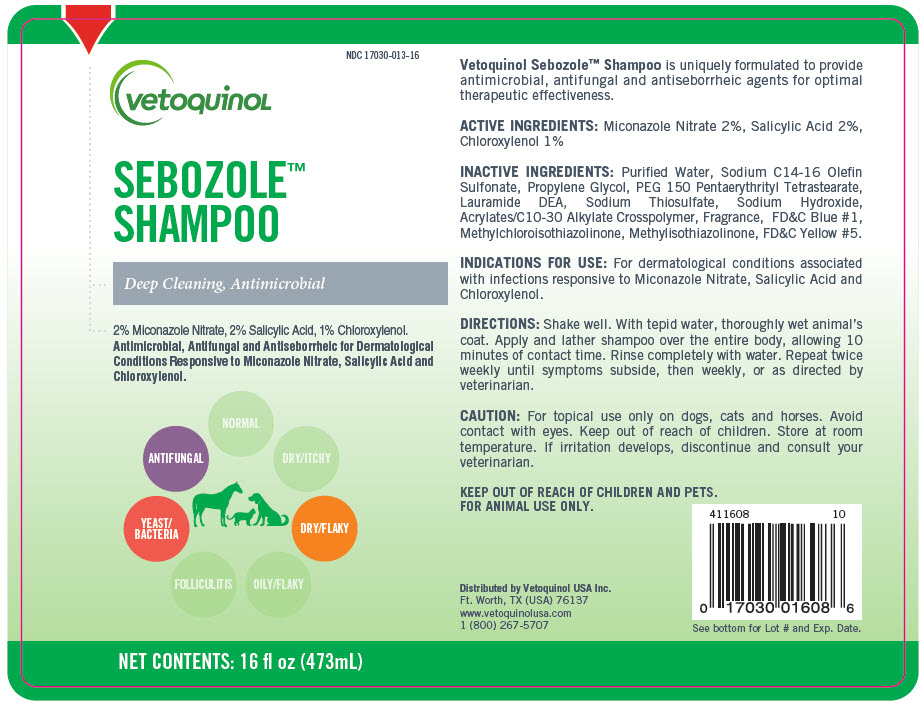 DRUG LABEL: Sebozole 
NDC: 17030-013 | Form: SHAMPOO
Manufacturer: Vetoquinol USA, Inc.
Category: animal | Type: OTC ANIMAL DRUG LABEL
Date: 20260106

ACTIVE INGREDIENTS: Miconazole Nitrate 20 mg/1 mL; SALICYLIC ACID 20 mg/1 mL; Chloroxylenol 10 mg/1 mL
INACTIVE INGREDIENTS: Water; Sodium C14-16 Olefin Sulfonate; PEG-150 Pentaerythrityl Tetrastearate; Lauric Diethanolamide; SODIUM THIOSULFATE ANHYDROUS; Propylene Glycol; Sodium Thiosulfate; CARBOMER HOMOPOLYMER, UNSPECIFIED TYPE; CARBOMER INTERPOLYMER TYPE A (ALLYL SUCROSE CROSSLINKED); Sodium Hydroxide; Methylchloroisothiazolinone; METHYLISOTHIAZOLINONE

Sebozole™ Shampoo
Deep Cleaning, Antimicrobial

VETERINARY INDICATIONS

Vetoquinol Sebozole™ Shampoo is uniquely formulated to provide antimicrobial, antifungal and antiseborrheic agents for optimal therapeutic effectiveness.

ACTIVE INGREDIENT

ACTIVE INGREDIENTS: Miconazole Nitrate 2%, Salicylic Acid 2%, Chloroxylenol 1%

INACTIVE INGREDIENT

INACTIVE INGREDIENTS: Purified Water, Sodium C14-16 Olefin Sulfonate, Propylene Glycol, PEG 150 Pentaerythrityl Tetrastearate, Lauramide DEA, Sodium Thiosulfate, Sodium Hydroxide, Acrylates/C10-30 Alkylate Crosspolymer, Fragrance, FD&C Blue #1, Methylchloroisothiazolinone, Methylisothiazolinone, FD&C Yellow #5.

INDICATIONS AND USAGE

INDICATIONS FOR USE: For dermatological conditions associated with infections responsive to Miconazole Nitrate, Salicylic Acid and Chloroxylenol.

DOSAGE AND ADMINISTRATION

DIRECTIONS: Shake well. With tepid water, thoroughly wet animal's coat. Apply and lather shampoo over the entire body, allowing 10 minutes of contact time. Rinse completely with water. Repeat twice weekly until symptoms subside, then weekly, or as directed by veterinarian.

PRECAUTIONS

CAUTION: For topical use only on dogs, cats and horses. Avoid contact with eyes. Keep out of reach of children. Store at room temperature. If irritation develops, discontinue and consult your veterinarian.

KEEP OUT OF REACH OF CHILDREN AND PETS.

FOR ANIMAL USE ONLY.

Distributed by Vetoquinol USA Inc.
Ft. Worth, TX (USA) 76137
www.vetoquinolusa.com
1 (800) 267-5707

PRINCIPAL DISPLAY PANEL - 473 mL Bottle Label

NDC 17030-013-16

vetoquinoL

SEBOZOLE™
SHAMPOO

Deep Cleaning, Antimicrobial

2% Miconazole Nitrate, 2% Salicylic Acid, 1% Chloroxylenol.
Antimicrobial, Antifungal and Antiseborrheic for Dermatological
Conditions Responsive to Miconazole Nitrate, Salicylic Acid and
Chloroxylenol.

ANTIFUNGAL
YEAST/
BACTERIA
DRY/FLAKY

NET CONTENTS: 16 fl oz (473mL)